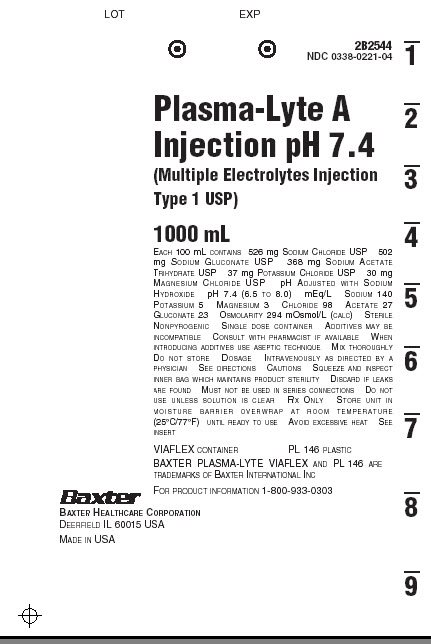 DRUG LABEL: Plasma-Lyte A
NDC: 0338-0221 | Form: INJECTION, SOLUTION
Manufacturer: Baxter Healthcare Corporation
Category: prescription | Type: HUMAN PRESCRIPTION DRUG LABEL
Date: 20190805

ACTIVE INGREDIENTS: SODIUM CHLORIDE 526 mg/100 mL; SODIUM GLUCONATE 502 mg/100 mL; SODIUM ACETATE 368 mg/100 mL; POTASSIUM CHLORIDE 37 mg/100 mL; MAGNESIUM CHLORIDE 30 mg/100 mL
INACTIVE INGREDIENTS: WATER; SODIUM HYDROXIDE

PLASMA-LYTE A Injection
pH 7.4 (Multiple Electrolytes Injection, Type 1, USP)
in VIAFLEX Plastic Container

DESCRIPTION

PLASMA-LYTE A Injection pH 7.4 (Multiple Electrolytes Injection, Type 1, USP) is a sterile, nonpyrogenic isotonic solution in a single dose container for intravenous administration. Each 100 mL contains 526 mg of Sodium Chloride, USP (NaCl); 502 mg of Sodium Gluconate (C6H11NaO7); 368 mg of Sodium Acetate Trihydrate, USP (C2H3NaO2•3H2O); 37 mg of Potassium Chloride, USP (KCl); and 30 mg of Magnesium Chloride, USP (MgCl2•6H2O). It contains no antimicrobial agents. The pH is adjusted with sodium hydroxide. The pH is 7.4 (6.5 to 8.0).

PLASMA-LYTE A Injection pH 7.4 (Multiple Electrolytes Injection, Type 1, USP) administered intravenously has value as a source of water, electrolytes, and calories. One liter has an ionic concentration of 140 mEq sodium, 5 mEq potassium, 3 mEq magnesium, 98 mEq chloride, 27 mEq acetate, and 23 mEq gluconate. The osmolarity is 294 mOsmol/L (calc). Normal physiologic osmolarity range is 280 to 310 mOsmol/L. The caloric content is 21 kcal/L.

The VIAFLEX plastic container is fabricated from a specially formulated polyvinyl chloride (PL 146 Plastic). The amount of water that can permeate from inside the container into the overwrap is insufficient to affect the solution significantly. Solutions in contact with the plastic container can leach out certain of its chemical components in very small amounts within the expiration period, e.g., di-2-ethylhexyl phthalate (DEHP), up to 5 parts per million. However, the safety of the plastic has been confirmed in tests in animals according to USP biological tests for plastic containers as well as by tissue culture toxicity studies.

CLINICAL PHARMACOLOGY

PLASMA-LYTE A Injection pH 7.4 (Multiple Electrolytes Injection, Type 1, USP) has value as a source of water and electrolytes. It is capable of inducing diuresis depending on the clinical condition of the patient.

PLASMA-LYTE A Injection pH 7.4 (Multiple Electrolytes Injection, Type 1, USP) produces a metabolic alkalinizing effect. Acetate and gluconate ions are metabolized ultimately to carbon dioxide and water, which requires the consumption of hydrogen cations.

INDICATIONS AND USAGE

PLASMA-LYTE A Injection pH 7.4 (Multiple Electrolytes Injection, Type 1, USP) is indicated as a source of water and electrolytes or as an alkalinizing agent.

CONTRAINDICATIONS

PLASMA-LYTE A Injection pH 7.4 (Multiple Electrolytes Injection, Type 1, USP) is contraindicated in patients with a known hypersensitivity to the product. See WARNINGS.

WARNINGS

Hypersensitivity Reactions

Hypersensitivity and infusion reactions have been reported with PLASMA-LYTE A Injection pH 7.4 (Multiple Electrolytes Injection, Type 1, USP). See ADVERSE REACTIONS.

Stop the infusion immediately if signs or symptoms of a hypersensitivity reaction develop, such as tachycardia, chest pain, dyspnea and flushing. Appropriate therapeutic countermeasures must be instituted as clinically indicated.

Electrolyte Imbalances

Fluid Overload

Depending on the volume and rate of infusion, the intravenous administration of PLASMA-LYTE A Injection pH 7.4 (Multiple Electrolytes Injection, Type 1, USP) can cause electrolyte disturbances such as overhydration, and congested states, including pulmonary congestion and edema.

Avoid PLASMA-LYTE A Injection pH 7.4 (Multiple Electrolytes Injection, Type 1, USP) in patients with or at risk for fluid and/or solute overloading. If use cannot be avoided, monitor fluid balance, electrolyte concentrations, and acid base balance, as needed and especially during prolonged use.

Hyponatremia

PLASMA-LYTE A Injection pH 7.4 (Multiple Electrolytes Injection, Type 1, USP) may cause hyponatremia. Hyponatremia can lead to acute hyponatremic encephalopathy characterized by headache, nausea, seizures, lethargy, and vomiting. Patients with brain edema are at particular risk of severe, irreversible and life-threatening brain injury.

The risk of hospital-acquired hyponatremia is increased in patients with cardiac or pulmonary failure, and in patients with non-osmotic vasopressin release (including SIADH) treated with high volume of hypotonic PLASMA-LYTE A Injection pH 7.4 (Multiple Electrolytes Injection, Type 1, USP).

Avoid PLASMA-LYTE A Injection pH 7.4 (Multiple Electrolytes Injection, Type 1, USP) in hypervolemic or overhydrated patients. If use cannot be avoided, monitor serum sodium concentrations.

Hypernatremia

Hypernatremia may occur with PLASMA-LYTE A Injection pH 7.4 (Multiple Electrolytes Injection, Type 1, USP)). Conditions that may increase the risk of hypernatremia, fluid overload and edema (central and peripheral), include patients with: primary hyperaldosteronism; secondary hyperaldosteronism associated with, for example, hypertension, congestive heart failure, liver disease (including cirrhosis), renal disease (including renal artery stenosis, nephrosclerosis); and pre-eclampsia.

Certain medications, such as corticosteroids or corticotropin, may also increase risk of sodium and fluid retention, see PRECAUTIONS.

Avoid PLASMA-LYTE A Injection pH 7.4 (Multiple Electrolytes Injection, Type 1, USP) in patients with, or at risk for, hypernatremia. If use cannot be avoided, monitor serum sodium concentrations.

Hypermagnesemia

Avoid solutions containing magnesium including PLASMA-LYTE A Injection pH 7.4 (Multiple Electrolytes Injection, Type 1, USP) in patients with or predisposed to hypermagnesemia, including patients with severe renal impairment and those patients receiving magnesium therapy (e.g., treatment of eclampsia and myasthenia gravis).

PLASMA-LYTE A Injection pH 7.4 (Multiple Electrolytes Injection, Type 1, USP) is not indicated for the treatment of hypomagnesemia.

Acidosis

PLASMA-LYTE A Injection pH 7.4 (Multiple Electrolytes Injection, Type 1, USP) is not for use for the treatment of lactic acidosis or severe metabolic acidosis in patients with severe liver and/or renal impairment.

Alkalosis

Excess administration of PLASMA-LYTE A Injection pH 7.4 (Multiple Electrolytes Injection, Type 1, USP) can result in metabolic alkalosis. Avoid PLASMA-LYTE A Injection pH 7.4 (Multiple Electrolytes Injection, Type 1, USP) in patients with alkalosis or at risk for alkalosis.

PLASMA-LYTE A Injection pH 7.4 (Multiple Electrolytes Injection, Type 1, USP) is not indicated for the treatment of hypochloremic hypokalemic alkalosis. Avoid use in patients with hypochloremic hypokalemic alkalosis.

Hypocalcemia

PLASMA-LYTE A Injection pH 7.4 (Multiple Electrolytes Injection, Type 1, USP) contains no calcium, and an increase in plasma pH due to its alkalinizing effect may lower the concentration of ionized (not protein-bound) calcium. Avoid PLASMA-LYTE A Injection pH 7.4 (Multiple Electrolytes Injection, Type 1, USP) in patients with hypocalcemia.

Hyperkalemia

Potassium-containing solutions, including PLASMA-LYTE A Injection pH 7.4 (Multiple Electrolytes Injection, Type 1, USP) may increase the risk of hyperkalemia.

Patient’s at increased risk of developing hyperkalemia include those:

- With conditions predisposing to hyperkalemia and/or associated with increased sensitivity to potassium, such as patients with severe renal impairment, acute dehydration, extensive tissue injury or burns, certain cardiac disorders such as congestive heart failure.
- Treated concurrently or recently with agents or products that cause or increase the risk of hyperkalemia (see PRECAUTIONS).

Avoid PLASMA-LYTE A Injection pH 7.4 (Multiple Electrolytes Injection, Type 1, USP) in patients with, or at risk for hyperkalemia. If use cannot be avoided, monitor serum potassium concentrations.

Although PLASMA-LYTE A Injection pH 7.4 (Multiple Electrolytes Injection, Type 1, USP) has a potassium concentration in plasma, it is insufficient to produce a useful effect in case of severe potassium deficiency; therefore, it is not indicated for correction of severe potassium deficiency.

PRECAUTIONS

Patients with Renal Impairment

In patients with renal impairment, administration of PLASMA-LYTE A Injection pH 7.4 (Multiple Electrolytes Injection, Type 1, USP) may result in sodium and/or potassium or magnesium retention (see WARNINGS). PLASMA-LYTE A Injection pH 7.4 (Multiple Electrolytes Injection, Type 1, USP) in patients with severe renal impairment or conditions that may cause sodium and/or potassium retention or magnesium retention, fluid overload, or edema. If use cannot be avoided, monitor patients with severe renal impairment for development of these adverse reactions.

Drug Interactions

Other Products that Affect Fluid and/or Electrolyte Balance

Administration of PLASMA-LYTE A Injection pH 7.4 (Multiple Electrolytes Injection, Type 1, USP) to patients treated concomitantly with drugs associated with sodium and fluid retention, may increase the risk of hypernatremia and volume overload. Avoid use of PLASMA-LYTE A Injection pH 7.4 (Multiple Electrolytes Injection, Type 1, USP) in patients receiving such products, such as corticosteroids or corticotropin. If use cannot be avoided, monitor serum electrolytes, fluid balance and acid-base balance.

Other Drugs that Increase the Risk of Hyponatremia

Administration of PLASMA-LYTE A Injection pH 7.4 (Multiple Electrolytes Injection, Type 1, USP) in patients treated concomitantly with medications associated with hyponatremia may increase the risk of developing hyponatremia.

Avoid use of PLASMA-LYTE A Injection pH 7.4 (Multiple Electrolytes Injection, Type 1, USP) in patients receiving products, such as diuretics, and certain antiepileptic and psychotropic medications. Drugs that increase the vasopressin effect reduce renal electrolyte free water excretion and may also increase the risk of hyponatremia following treatment with intravenous fluids. If use cannot be avoided, monitor serum sodium concentrations.

Lithium

Renal clearance of lithium may be increased during administration of PLASMA-LYTE A Injection pH 7.4 (Multiple Electrolytes Injection, Type 1, USP). Monitor serum lithium concentrations during concomitant use.

Other Products that Increase the Risk of Hyperkalemia

Because of its potassium content, avoid use of PLASMA-LYTE A Injection pH 7.4 (Multiple Electrolytes Injection, Type 1, USP) in patients receiving products that can cause hyperkalemia or increase the risk of hyperkalemia, such as potassium sparing diuretics, ACE inhibitors, angiotensin II receptor antagonists, or the immunosuppressants tacrolimus and cyclosporine. If use cannot be avoided, monitor serum potassium concentrations.

Drugs with pH Dependent Renal Elimination

Due to its alkalinizing effect (formation of bicarbonate), PLASMA-LYTE A Injection pH 7.4 (Multiple Electrolytes Injection, Type 1, USP) may interfere with the elimination of drugs with pH dependent renal elimination. Renal clearance of acidic drugs may be increased. Renal clearance of alkaline drugs may be decreased.

Drug/Laboratory Test Interactions

There have been reports of positive test results using the Bio-Rad Laboratories Platelia Aspergillus EIA test in patients receiving Baxter gluconate containing PLASMA-LYTE solutions. These patients were subsequently found to be free of Aspergillus infection. Therefore, positive test results for this test in patients receiving Baxter gluconate containing PLASMA-LYTE solutions should be interpreted cautiously and confirmed by other diagnostic methods.

Carcinogenesis, Mutagenesis, Impairment of Fertility

Studies with PLASMA-LYTE A Injection pH 7.4 (Multiple Electrolytes Injection, Type 1, USP) have not been performed to evaluate carcinogenic potential, mutagenic potential, or effects on fertility.

Pregnancy

Teratogenic Effects

Animal reproduction studies have not been conducted with PLASMA-LYTE A Injection pH 7.4 (Multiple Electrolytes Injection, Type 1, USP). It is also not known whether PLASMA-LYTE A Injection pH 7.4 (Multiple Electrolytes Injection, Type 1, USP) can cause fetal harm when administered to a pregnant woman or can affect reproduction capacity. PLASMA-LYTE A Injection pH 7.4 (Multiple Electrolytes Injection, Type 1, USP) should be given to a pregnant woman only if clearly needed.

Nursing Mothers

It is not known whether this drug is excreted in human milk. Because many drugs are excreted in human milk, caution should be exercised when PLASMA-LYTE A Injection pH 7.4 (Multiple Electrolytes Injection, Type 1, USP) is administered to a nursing mother.

Pediatric Use

The use of PLASMA-LYTE A Injection pH 7.4 (Multiple Electrolytes Injection, Type 1, USP) in pediatric patients is based on clinical practice.

Geriatric Use

Geriatric patients are at increased risk of developing electrolyte imbalances. PLASMA-LYTE A Injection pH 7.4 (Multiple Electrolytes Injection, Type 1, USP) is known to be substantially excreted by the kidney, and the risk of toxic reactions to this drug may be greater in patients with impaired renal function. Therefore, dose selection for an elderly patient should be cautious, usually starting at the low end of the dosing range, reflecting the greater frequency of decreased hepatic, renal, or cardiac function, and of concomitant disease or other drug therapy. Consider monitoring renal function in elderly patients.

ADVERSE REACTIONS

Post-Marketing Adverse Reactions

The following adverse reactions associated with the use of PLASMA-LYTE A Injection pH 7.4 (Multiple Electrolytes Injection, Type 1, USP) were identified in clinical trials or postmarketing reports. Because postmarketing reactions were reported voluntarily from a population of uncertain size, it is not always possible to estimate their frequency, reliably, or to establish a causal relationship to drug exposure.

Hypersensitivity and Infusion Reactions: tachycardia, chest pain, chest discomfort, dyspnea, flushing, hyperemia, asthenia, pyrexia, hypotension, wheezing, urticaria, cold sweat, chills.

General Disorders and Administration Site Conditions: infusion site pain, burning sensation.

Metabolism and nutrition disorders: hyperkalemia, hyponatremia.

Nervous System Disorders: hyponatremic encephalopathy.

Overdose

Excessive administration of PLASMA-LYTE A Injection pH 7.4 (Multiple Electrolytes Injection, Type 1, USP) can cause:

- fluid overload with a risk of edema (peripheral and/or pulmonary), particularly when renal sodium excretion is impaired.
- hypernatremia and hyperkalemia, especially in patients with severe renal impairment.
- hypermagnesemia. See WARNINGS and ADVERSE REACTIONS
- metabolic alkalosis with or without hypokalemia and decreased ionized serum calcium and magnesium concentrations.

When assessing an overdose, any additives in the solution must also be considered.

The effects of an overdose may require immediate medical attention and treatment.

Interventions include discontinuation of PLASMA-LYTE A Injection pH 7.4 (Multiple Electrolytes Injection, Type 1, USP), dose reduction, and other measures as indicated for the specific clinical constellation (e.g., monitoring of fluid balance, electrolyte concentrations and acid base balance).

DOSAGE AND ADMINISTRATION

Important Administration Instructions

- PLASMA-LYTE A Injection pH 7.4 (Multiple Electrolytes Injection, Type 1, USP) is intended for intravenous administration using sterile equipment.
- Do not connect flexible plastic containers in series in order to avoid air embolism due to possible residual air contained in the primary container.
- Set the vent to the closed position on a vented intravenous administration set to prevent air embolism.
- Use a dedicated line without any connections to avoid air embolism.
- Do not pressurize intravenous solutions contained in flexible plastic containers to increase flow rates in order to avoid air embolism due to incomplete evacuation of residual air in the container.
- Prior to infusion, visually inspect the solution for particulate matter and discoloration. The solution should be clear and there should be no precipitates. Do not administer unless solution is clear, and container is undamaged.
- PLASMA-LYTE A Injection pH 7.4 (Multiple Electrolytes Injection, Type 1, USP) is compatible with blood or blood components. It may be administered prior to or following the infusion of blood through the same administration set (i.e., as a priming solution), added to or infused concurrently with blood components, or used as a diluent in the transfusion of packed erythrocytes. PLASMA-LYTE A Injection and 0.9% Sodium Chloride Injection, USP are equally compatible with blood or blood components.

Dosing Information

The choice of product, dosage, volume, rate, and duration of administration is dependent upon the age, weight and clinical condition of the patient and concomitant therapy, and administration should be determined by a physician experienced in intravenous fluid therapy.

Introduction of Additives

Additives may be incompatible.

Evaluate all additions to the plastic container for compatibility and stability of the resulting preparation. Consult with a pharmacist, if available.

If, in the informed judgment of the physician, it is deemed advisable to introduce additives, use aseptic technique. Mix thoroughly when additives have been introduced. After addition, if there is a discoloration and/or the appearance of precipitates, insoluble complexes or crystals, do not use. Do not store solutions containing additives. Discard any unused portion.

HOW SUPPLIED

PLASMA-LYTE A Injection pH 7.4 (Multiple Electrolytes Injection, Type 1, USP) in VIAFLEX plastic containers is available as shown below:

Code | Size (mL) | NDC
2B2544 | 1000 | NDC 0338-0221-04
2B2543 | 500 | NDC 0338-0221-03

Exposure of pharmaceutical products to heat should be minimized. Avoid excessive heat. It is recommended the product be stored at room temperature (25°C); brief exposure up to 40°C does not adversely affect the product.

DIRECTIONS FOR USE OF VIAFLEX PLASTIC CONTAINER

For Information on Risk of Air Embolism – see DOSAGE AND ADMINISTRATION

To Open

Tear overwrap down side at slit and remove solution container. Visually inspect the container. If the outlet port protector is damaged, detached, or not present, discard container as solution path sterility may be impaired. Some opacity of the plastic due to moisture absorption during the sterilization process may be observed. This is normal and does not affect the solution quality or safety. The opacity will diminish gradually. Check for minute leaks by squeezing inner bag firmly. If leaks are found, discard solution as sterility may be impaired. If supplemental medication is desired, follow directions below.

Preparation for Administration

1. Suspend container from eyelet support.
2. Remove protector from outlet port at bottom of container.
3. Attach administration set. Refer to complete directions accompanying set.

To add medication before solution administration

1. Prepare medication site.
2. Using syringe with 19 to 22 gauge needle, puncture resealable medication port and inject.
3. Mix solution and medication thoroughly. For high density medication such as potassium chloride, squeeze ports while ports are upright and mix thoroughly.

To add medication during solution administration

1. Close clamp on the set.
2. Prepare medication site.
3. Using syringe with 19 to 22 gauge needle, puncture resealable medication port and inject.
4. Remove container from IV pole and/or turn to an upright position.
5. Evacuate both ports by squeezing them while container is in the upright position.
6. Mix solution and medication thoroughly.
7. Return container to in use position and continue administration.

Baxter Healthcare Corporation
Deerfield, IL 60015 USA

Printed in USA

07-19-00-1559

Rev. August 2019

Baxter, Plasma-Lyte, Viaflex, and PL 146 are trademarks of Baxter International Inc.

PACKAGE LABEL - PRINCIPAL DISPLAY PANEL

Plasma-Lyte A Injection pH 7.4 (Multiple Electrolytes Injection Type 1 USP) 1000mL Container Label

Plasma-Lyte A Injection pH 7.4 (Multiple Electrolytes Injection Type 1 USP) 1000mL Container Label

2B2544

NDC 0338-0221-04

Plasma-Lyte A

Injection pH 7.4

(Multiple Electrolytes Injection

Type 1 USP)

1000 mL

Each 100 mL contains 526 mg Sodium Chloride USP 502

mg Sodium Gluconate USP 368 mg Sodium Acetate

Trihydrate USP 37 mg Potassium Chloride USP 30 mg

Magnesium Chloride USP pH adjusted with Sodium

Hydroxide ph 7.4 (6.5 to 8.0) mEq/L Sodium 140

Potassium 5 Magnesium 3 Chloride 98 Acetate 27

Gluconate 23 Osmolarity 294 mOsmol/L (calc) Sterile

Nonpyrogenic Single dose container Additives may be

incompatible Consult with pharmacist if available When

introducing additives use aseptic technique Mix thoroughly

Do not store Dosage Intravenously as directed by a

physician See directions Cautions Squeeze and inspect

inner bag which maintains product sterility Discard if leaks

are found Must not be used in series connections Do not

use unless solution is clear Rx Only Store unit in

moisture barrier overwrap at room temperature

(25°C/77°F) until ready to use Avoid excessive heat See

insert

VIAFLEX container PL 146 plastic

BAXTER PLASMA-LYTE VIAFLEX and PL 146 are

trademarks of Baxter International Inc

For product information 1-800-933-0303

Baxter

Baxter Healthcare Corporation

Deerfield IL 60015 USA

Made in USA